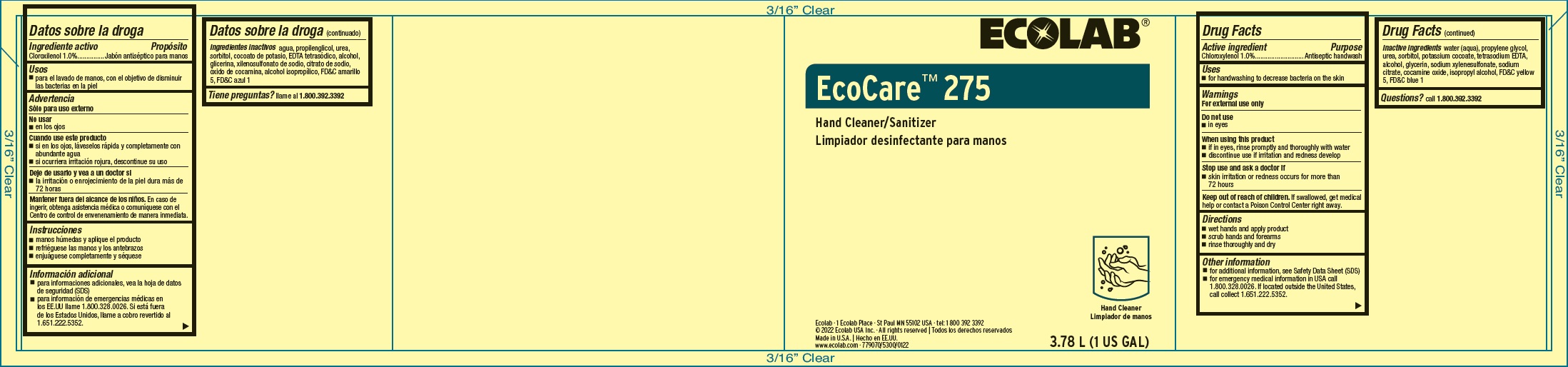 DRUG LABEL: EcoCare 275
NDC: 47593-493 | Form: SOLUTION
Manufacturer: Ecolab Inc.
Category: otc | Type: HUMAN OTC DRUG LABEL
Date: 20240506

ACTIVE INGREDIENTS: CHLOROXYLENOL 100 mg/1 mL
INACTIVE INGREDIENTS: WATER; PROPYLENE GLYCOL; UREA; SORBITOL; POTASSIUM COCOATE; EDETATE SODIUM; ALCOHOL; GLYCERIN; SODIUM XYLENESULFONATE; SODIUM CITRATE; COCAMINE OXIDE; ISOPROPYL ALCOHOL; FD&C YELLOW NO. 5; FD&C BLUE NO. 1

Drug Facts

Active Ingredient

Chloroxylenol, 1.0%

Purpose

Antiseptic handwash

Uses

- for handwashing to decrease bacteria on the skin

Warnings

For external use only

Do not use

- in eyes

When using this product

- if in eyes, rinse promptly and thoroughly with water
- discontinue use if irritation and redness develop

Stop use and ask a doctor if

- skin irritation or redness persists for more than 72 hours

Keep out of reach of children. If swallowed, get medical help or contact a Poison Control Center right away.

Directions

- wet hands and apply product
- scrub hands and forearms
- rinse throughly and dry

Other information

- for additional information, see Safety Data Sheet (SDS)
- for emergency medical information in USA call 1.800.328.0026. If located outside the United States, call collect 1.651.222.5352.

INACTIVE INGREDIENT

Inactive ingredients water (aqua), propylene glycol, urea, sorbitol, potassium cocoate, tetrasodium EDTA, alcohol, glycerin, sodium xylenesulfonate, sodium citrate, cocamine oxide, isopropyl alcohol, FD&C yellow 5, FD&C blue 1

Questions?

Call 1.800.392.3392

Principal Display Panel

ECOLAB®
EcoCare™ 275
Hand Cleaner/Sanitizer

3.78 L (1 US GAL)

Ecolab · 1 Ecolab Place · St. Paul MN 55102 USA · tel: 1 800 392 3392

© 2022 Ecolab USA Inc. · All rights reserved

Made in U.S.A.

www.ecolab.com · 779070/5300/0122